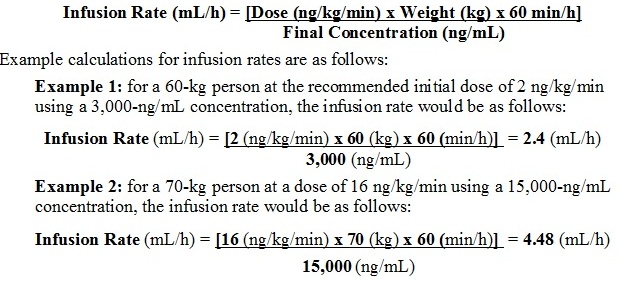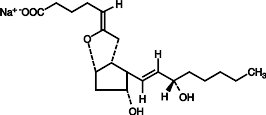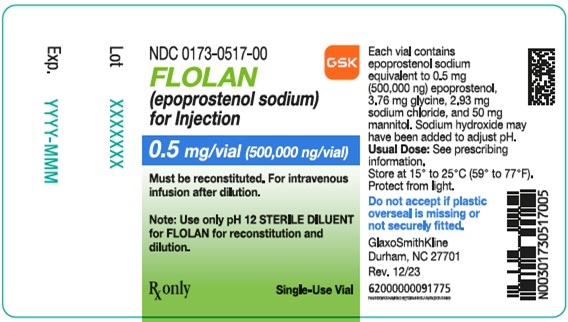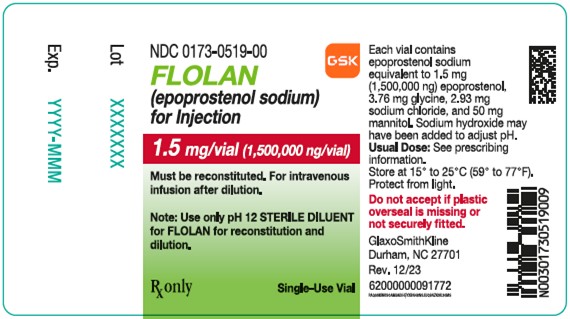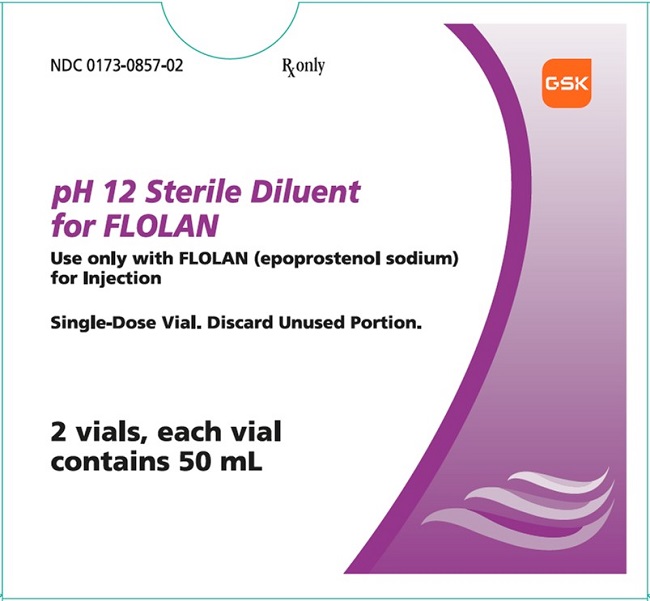 DRUG LABEL: FLOLAN
NDC: 0173-0517 | Form: INJECTION, POWDER, LYOPHILIZED, FOR SOLUTION
Manufacturer: GlaxoSmithKline LLC
Category: prescription | Type: HUMAN PRESCRIPTION DRUG LABEL
Date: 20231026

ACTIVE INGREDIENTS: EPOPROSTENOL SODIUM 0.5 mg/1 1
INACTIVE INGREDIENTS: GLYCINE; SODIUM CHLORIDE; MANNITOL

HIGHLIGHTS OF PRESCRIBING INFORMATION

These highlights do not include all the information needed to use FLOLAN safely and effectively. See full prescribing information for FLOLAN.
FLOLAN (epoprostenol sodium) for injection, for intravenous use
Initial U.S. Approval: 1995

1 INDICATIONS AND USAGE

FLOLAN is a prostacyclin vasodilator indicated for the treatment of pulmonary arterial hypertension (PAH) (WHO Group I) to improve exercise capacity. Studies establishing effectiveness included predominantly (97%) patients with NYHA Functional Class III-IV symptoms and etiologies of idiopathic or heritable PAH (49%) or PAH associated with connective tissue diseases (51%). (1)

2 DOSAGE AND ADMINISTRATION

- Initiate intravenous infusion through a central venous catheter at 2 ng/kg/min. (2.2, 2.3)
- Change dose in 1- to 2-ng/kg/min increments at intervals of at least 15 minutes based on clinical response. (2.2)
- Avoid sudden large dose reductions. (2.2, 5.2)

3 DOSAGE FORMS AND STRENGTHS

For injection: 0.5 mg or 1.5 mg of epoprostenol freeze-dried powder in a single-dose vial for reconstitution with the supplied diluent. (3)

4 CONTRAINDICATIONS

- Heart failure with reduced ejection fraction. (4)
- Hypersensitivity to FLOLAN or any of its ingredients. (4)

5 WARNINGS AND PRECAUTIONS

- Pulmonary edema: Discontinue therapy if pulmonary edema occurs. (5.1)
- Rebound pulmonary hypertension: Do not abruptly discontinue or decrease the dose. (5.2)
- Vasodilation reactions: Monitor blood pressure and symptoms regularly during initiation and after dose change. (5.3)
- Increased risk for bleeding: Increased risk for hemorrhagic complications, particularly for patients with other risk factors for bleeding. (5.4)

6 ADVERSE REACTIONS

The most common adverse reactions are dizziness, jaw pain, headache, musculoskeletal pain, and nausea/vomiting, and are generally associated with vasodilation. (6)

To report SUSPECTED ADVERSE REACTIONS, contact GlaxoSmithKline at 1-888-825-5249 or FDA at 1-800-FDA-1088 or www.fda.gov/medwatch.

FULL PRESCRIBING INFORMATION

1 INDICATIONS AND USAGE

FLOLAN is indicated for the treatment of pulmonary arterial hypertension (PAH) (WHO Group I) to improve exercise capacity. Trials establishing effectiveness included predominantly (97%) patients with New York Heart Association (NYHA) Functional Class III-IV symptoms and etiologies of idiopathic or heritable PAH (49%) or PAH associated with connective tissue diseases (51%).

2 DOSAGE AND ADMINISTRATION

2.1 Reconstitution

Each vial is for single use only; discard any unused diluent or unused reconstituted solution.

Select a concentration for the solution of FLOLAN that is compatible with the infusion pump being used with respect to minimum and maximum flow rates, reservoir capacity, and the infusion pump criteria listed below [see Dosage and Administration (2.3)].

Using aseptic technique, reconstitute FLOLAN only with pH 12 STERILE DILUENT for FLOLAN. Table 1 gives directions for preparing several different concentrations of FLOLAN. See storage and administration time limits for the reconstituted FLOLAN below.

Table 1. Reconstitution and Dilution Instructions for FLOLAN Using pH 12 STERILE DILUENT for FLOLAN.
To make 100 mL of solution with final concentration of: | Directions:
3,000 ng/mL | Dissolve contents of one 0.5‑mg vial with 5 mL of sterile diluent. Withdraw 3 mL and add to sufficient sterile diluent to make a total of 100 mL.
5,000 ng/mL | Dissolve contents of one 0.5‑mg vial with 5 mL of sterile diluent. Withdraw entire vial contents and add sufficient sterile diluent to make a total of 100 mL.
10,000 ng/mL | Dissolve contents of two 0.5‑mg vials each with 5 mL of sterile diluent. Withdraw entire vial contents and add sufficient sterile diluent to make a total of 100 mL.
15,000 ng/mLa | Dissolve contents of one 1.5‑mg vial with 5 mL of sterile diluent. Withdraw entire vial contents and add sufficient sterile diluent to make a total of 100 mL.
a Higher concentrations may be prepared for patients who receive FLOLAN long-term.

Storage and Administration Limits for Reconstituted FLOLAN

- Freshly prepared reconstituted solutions or reconstituted solutions that have been stored at 2°C to 8°C (36°F to 46°F) for no longer than 8 days can be administered up to:
- 48 hours at up to 25°C (77°F).
  - 36 hours at up to 30°C (86°F).
  - 24 hours at up to 35°C (95°F).
  - 12 hours at up to 40°C (104°F).
Discard any unused solution after these times.
- Reconstituted solutions can be used immediately. Refrigerate at 2°C to 8°C (36°F to 46°F) if not used immediately.
- Protect from light.
- Do not freeze reconstituted solutions.

2.2 Dosage

Initiate intravenous infusions of FLOLAN at 2 ng/kg/min. Alter the infusion by 1- to 2-ng/kg/min increments at intervals sufficient to allow assessment of clinical response. These intervals should be at least 15 minutes.

During dose initiation, asymptomatic increases in pulmonary artery pressure coincident with increases in cardiac output may occur. In such cases, consider dose reduction, but such an increase does not imply that chronic treatment is contraindicated.

Base changes in the chronic infusion rate on persistence, recurrence, or worsening of the patient's symptoms of pulmonary hypertension and the occurrence of adverse vasodilatory reactions. In general, expect progressive increases in dose.

If dose-related adverse reactions occur, make dose decreases gradually in 2-ng/kg/min decrements every 15 minutes or longer until the dose-limiting effects resolve [see Adverse Reactions (6.1, 6.2)]. Avoid abrupt withdrawal of FLOLAN or sudden large reductions in infusion rates [see Warnings and Precautions (5.2)].

Following establishment of a new chronic infusion rate, measure standing and supine blood pressure for several hours.

Taper doses of FLOLAN after initiation of cardiopulmonary bypass in patients receiving lung transplants.

2.3 Administration

Initiate FLOLAN in a setting with adequate personnel and equipment for physiologic monitoring and emergency care.

Inspect parenteral drug products for particulate matter and discoloration prior to administration whenever solution and container permit. If either particulate matter or discoloration is noted, do not use.

Administer continuous chronic infusion of FLOLAN through a central venous catheter. Temporary peripheral intravenous infusion may be used until central access is established. Do not administer bolus injections of FLOLAN.

The ambulatory infusion pump used to administer FLOLAN should: (1) be small and lightweight, (2) be able to adjust infusion rates in 2‑ng/kg/min increments, (3) have occlusion, end-of-infusion, and low-battery alarms, (4) be accurate to ± 6% of the programmed rate, and (5) be positive-pressure‑driven (continuous or pulsatile) with intervals between pulses not exceeding 3 minutes at infusion rates used to deliver FLOLAN. The reservoir should be made of polyvinyl chloride, polypropylene, or glass. Use a 60-inch microbore non-di-(2-ethylhexyl)phthalate (DEHP) extension set with proximal antisyphon valve, low-priming volume (0.9 mL), and in-line 0.22-micron filter.

Preparation and administration materials containing polyethylene terephthalate (PET) or polyethylene terephthalate glycol (PETG) may become damaged when used with FLOLAN prepared with pH 12 STERILE DILUENT for FLOLAN and therefore must not be used.

Consult the manufacturer of the sets to confirm that they are considered compatible with highly alkaline solutions, such as FLOLAN prepared with pH 12 STERILE DILUENT for FLOLAN.

To avoid interruptions in drug delivery, the patient should have access to a backup infusion pump and intravenous infusion sets.

Do not administer or dilute reconstituted solutions of FLOLAN with other parenteral solutions or medications. Consider a multi‑lumen catheter if other intravenous therapies are routinely administered.

Select a concentration for the solution of FLOLAN that is compatible with the infusion pump being used with respect to minimum and maximum flow rates, reservoir capacity, and the infusion pump criteria listed above. When administered chronically, prepare FLOLAN in a drug delivery reservoir appropriate for the infusion pump with a total reservoir volume of at least 100 mL, using 2 vials of pH 12 STERILE DILUENT for FLOLAN.

Generally, 3,000 ng/mL and 10,000 ng/mL are satisfactory concentrations to deliver between 2 to 16 ng/kg/min in adults. Higher infusion rates, and therefore, more concentrated solutions may be necessary with long‑term administration of FLOLAN.

Infusion rates may be calculated using the following formula:

3 DOSAGE FORMS AND STRENGTHS

For injection: 0.5 mg or 1.5 mg of epoprostenol, freeze-dried powder in a single-dose vial for reconstitution with the supplied diluent.

4 CONTRAINDICATIONS

FLOLAN is contraindicated in patients with heart failure caused by reduced left ventricular ejection fraction [see Clinical Studies (14.3)].

FLOLAN is contraindicated in patients with a hypersensitivity to the drug or any of its ingredients.

5 WARNINGS AND PRECAUTIONS

5.1 Pulmonary Edema

If the patient develops pulmonary edema during initiation with FLOLAN, discontinue therapy and do not readminister. Consider the possibility of associated pulmonary veno-occlusive disease in such patients.

5.2 Rebound Pulmonary Hypertension following Abrupt Withdrawal

Avoid abrupt withdrawal (including interruptions in drug delivery) or sudden large reductions in dosage of FLOLAN because symptoms associated with rebound pulmonary hypertension (e.g., dyspnea, dizziness, and asthenia) may occur. In clinical trials, one Class III patient's death was judged attributable to the interruption of FLOLAN.

5.3 Vasodilation

FLOLAN is a potent pulmonary and systemic vasodilator and can cause hypotension and other reactions such as flushing, nausea, vomiting, dizziness, and headache. Monitor blood pressure and symptoms regularly during initiation and after dose change [see Dosage and Administration (2.2)].

5.4 Increased Risk for Bleeding

FLOLAN is a potent inhibitor of platelet aggregation. Therefore, expect an increased risk for hemorrhagic complications, particularly for patients with other risk factors for bleeding [see Clinical Pharmacology (12.3)].

6 ADVERSE REACTIONS

6.1 Clinical Trials Experience

Because clinical trials are conducted under widely varying conditions, adverse reaction rates observed in the clinical trials of a drug cannot be directly compared with rates in the clinical trials of another drug and may not reflect the rates observed in practice.

Adverse reactions are shown in Table 2 and are generally related to vasodilatory effects.

Table 2. Adverse Reactions Occurring in Patients with Idiopathic or Heritable PAH and with PAH Associated with Scleroderma Spectrum of Diseases (PAH/SSD) Occurring ≥10% More Frequently on FLOLAN than Conventional Therapy
Adverse Reaction | Idiopathic or Heritable; PAH |  | PAH/SSD
Adverse Reaction | FLOLAN | Conventional Therapy | FLOLAN | Conventional Therapy
Adverse Reaction | (n = 52) | (n = 54) | (n = 56) | (n = 55)
Body as a whole
Jaw pain | 54% | 0% | 75% | 0%
Nonspecific musculoskeletal pain | 35% | 15% | 84% | 65%
Headache | 83% | 33% | 46% | 5%
Chills/fever/sepsis/flu-like symptoms | 25% | 11% | 13% | 11%
Cardiovascular system
Flushing | 42% | 2% | 23% | 0%
Hypotension | 27% | 31% | 13% | 0%
Tachycardia | 35% | 24% | 43% | 42%
Digestive system
Anorexia | 25% | 30% | 66% | 47%
Nausea/Vomiting | 67% | 48% | 41% | 16%
Diarrhea | 37% | 6% | 50% | 5%
Skin and Appendages
Skin ulcer | - | - | 39% | 24%
Eczema/rash/urticaria | 10% | 13% | 25% | 4%
Musculoskeletal System
Myalgia | 44% | 31% | - | -
Nervous system
Anxiety/hyperkinesias/nervousness/tremor | 21% | 9% | 7% | 5%
Hyperesthesia/hypesthesia/paresthesia | 12% | 2% | 5% | 0%
Dizziness | 83% | 70% | 59% | 76%

PAH = Pulmonary Arterial Hypertension, SSD = Scleroderma Spectrum of Diseases.

Adverse Events Attributable to the Drug Delivery System

Chronic infusions of FLOLAN are delivered using a small, portable infusion pump through an indwelling central venous catheter. During controlled PAH trials of up to 12 weeks’ duration, the local infection rate was about 18% and the rate for pain was about 11%. During long‑term follow‑up, sepsis was reported at a rate of 0.3 infections/patient per year in patients treated with FLOLAN.

6.2 Postmarketing Experience

The following events have been identified during postapproval use of FLOLAN. Because these reactions are reported voluntarily from a population of uncertain size, it is not always possible to estimate reliably their frequency or establish a causal relationship to drug exposure.

Blood and Lymphatic

Anemia, hypersplenism, pancytopenia, splenomegaly, thrombocytopenia.

Cardiac

High output cardiac failure.

Endocrine and Metabolic

Hyperthyroidism.

Gastrointestinal

Hepatic failure.

Respiratory, Thoracic, and Mediastinal

Pulmonary embolism.

8 USE IN SPECIFIC POPULATIONS

8.1 Pregnancy

Risk Summary

Limited published data from case series and case reports have not established an association with FLOLAN and major birth defects, miscarriage or adverse maternal or fetal outcomes when FLOLAN is used during pregnancy. There are risks to the mother and fetus from untreated pulmonary arterial hypertension (see Clinical Considerations). In animal reproduction studies, pregnant rats and rabbits received epoprostenol sodium during organogenesis at exposures of 2.5 and 4.8 times the maximum recommended human dose (MRHD), respectively, and there was no effect on the fetus (see Data).

The estimated background risk of major birth defects and miscarriage for the indicated population is unknown. All pregnancies have a background risk of birth defect, loss, or other adverse outcomes. In the U.S. general population, the estimated background risk of major birth defects and miscarriage in clinically recognized pregnancies is 2% to 4% and 15% to 20%, respectively.

Clinical Considerations

Disease-Associated Maternal and/or Embryo/Fetal Risk: Pregnant women with untreated pulmonary arterial hypertension are at risk for heart failure, stroke, preterm delivery, and maternal and fetal death.

Data

Animal Data: Embryo-fetal development studies have been performed in rats and rabbits during organogenesis. Epoprostenol sodium doses up to 100 mcg/kg/day, a dose that was maternally toxic in rabbits but not in rats (600 mcg/m^2/day in rats, 2.5 times the MRHD, and 1,180 mcg/m^2/day in rabbits, 4.8 times the MRHD based on body surface area), had no effect on the fetus.

In a postnatal development study, epoprostenol sodium was administered subcutaneously to female rats for 2 weeks prior to mating through weaning and to male rats for 60 days prior to and through mating at a male and female toxic dose of up to 100 mcg/kg/day (600 mcg/m^2/day, 2.5 times the MRHD based on body surface area). There was no effect on growth and development of the offspring.

8.2 Lactation

Risk Summary

There are no data on the presence of epoprostenol in either human or animal milk, the effects on the breastfed infant, or the effect on milk production.

The developmental and health benefits of breastfeeding should be considered along with the mother’s clinical need for FLOLAN and any potential adverse effects on the breastfed child from epoprostenol or from the underlying maternal condition.

8.4 Pediatric Use

Safety and effectiveness in pediatric patients have not been established.

8.5 Geriatric Use

Clinical trials of FLOLAN in pulmonary hypertension did not include sufficient numbers of subjects aged 65 and over to determine whether they respond differently from younger subjects. Other reported clinical experience has not identified differences in responses between the elderly and younger patients. In general, dose selection for an elderly patient should be cautious, usually starting at the low end of the dosing range, reflecting the greater frequency of decreased hepatic, renal, or cardiac function and of concomitant disease or other drug therapy.

10 OVERDOSAGE

Signs and Symptoms

Hypoxemia, hypotension, and respiratory arrest leading to death have been reported in clinical practice following overdosage of FLOLAN.

Excessive doses of FLOLAN were associated with flushing, headache, hypotension, tachycardia, nausea, vomiting, and diarrhea during clinical trials.

One patient with PAH/SSD accidentally received 50 mL of an unspecified concentration of FLOLAN. The patient vomited and became unconscious with an initially unrecordable blood pressure. FLOLAN was discontinued and the patient regained consciousness within seconds.

Single intravenous doses of FLOLAN at 10 and 50 mg/kg (2,703 and 27,027 times the recommended acute phase human dose based on body surface area) were lethal to mice and rats, respectively. Symptoms of acute toxicity were hypoactivity, ataxia, loss of righting reflex, deep slow breathing, and hypothermia.

Treatment

Discontinue or reduce dose of FLOLAN.

11 DESCRIPTION

FLOLAN (epoprostenol sodium) for injection is sterile sodium salt that is a white or off-white powder formulated for intravenous (IV) administration. Each vial of FLOLAN contains epoprostenol sodium equivalent to either 0.5 mg (500,000 ng) or 1.5 mg (1,500,000 ng) epoprostenol, 3.76 mg glycine, 50 mg mannitol, and 2.93 mg sodium chloride. Sodium hydroxide may have been added to adjust pH.

Epoprostenol (PGI2, PGX, prostacyclin), a metabolite of arachidonic acid, is a naturally occurring prostaglandin with potent vasodilatory activity and inhibitory activity of platelet aggregation. The chemical name of epoprostenol is (5Z,9α,11α,13E,15S)-6,9-epoxy-11,15-dihydroxyprosta-5,13-dien-1-oic acid. Epoprostenol sodium has a molecular weight of 374.45 and a molecular formula of C20H31NaO5. The structural formula is:

FLOLAN must be reconstituted with pH 12 STERILE DILUENT for FLOLAN.

pH 12 STERILE DILUENT for FLOLAN is supplied in plastic vials each containing 50 mL of 94 mg glycine, 73.3 mg sodium chloride, sodium hydroxide (added to adjust the pH to 11.7 to 12.3), and Water for Injection. The stability of reconstituted solutions of FLOLAN is pH-dependent and is greater at higher pH.

12 CLINICAL PHARMACOLOGY

12.1 Mechanism of Action

Epoprostenol has 2 major pharmacological actions: (1) direct vasodilation of pulmonary and systemic arterial vascular beds and (2) inhibition of platelet aggregation.

12.2 Pharmacodynamics

Acute Hemodynamic Effects

Acute intravenous infusions of FLOLAN for up to 15 minutes in patients with idiopathic or heritable PAH or PAH/SSD produce dose‑related increases in cardiac index (CI) and stroke volume (SV) and dose‑related decreases in pulmonary vascular resistance (PVR), total pulmonary resistance (TPR), and mean systemic arterial pressure (SAPm). The effects of FLOLAN on mean pulmonary artery pressure (PAPm) were variable and minor.

In humans, hemodynamic changes due to epoprostenol (e.g., increased heart rate, facial flushing) returned to baseline within 10 minutes of termination of 60-minute infusions of 1 to 16 ng/kg/min. This pharmacodynamic behavior is consistent with a short in vivo half-life and rapid clearance in humans, as suggested by the results of animal and in vitro studies.

In animals, the vasodilatory effects reduce right- and left-ventricular afterload and increase cardiac output and stroke volume. The effect of epoprostenol on heart rate in animals varies with dose. At low doses, there is vagally-mediated bradycardia, but at higher doses, epoprostenol causes reflex tachycardia in response to direct vasodilation and hypotension. No major effects on cardiac conduction have been observed. Additional pharmacologic effects of epoprostenol in animals include bronchodilation, inhibition of gastric acid secretion, and decreased gastric emptying.

Drug Interaction Studies

Additional reductions in blood pressure may occur when FLOLAN is administered with diuretics, antihypertensive agents, or other vasodilators.

When other antiplatelet agents or anticoagulants are used concomitantly, there is a potential for FLOLAN to increase the risk of bleeding. However, patients receiving infusions of FLOLAN in clinical trials were maintained on anticoagulants without evidence of increased bleeding.

12.3 Pharmacokinetics

Absorption/Distribution

Epoprostenol is rapidly hydrolyzed at neutral pH in blood and is also subject to enzymatic degradation. No available chemical assay is sufficiently sensitive and specific to assess the in vivo human pharmacokinetics of epoprostenol. Animal studies using tritium‑labeled epoprostenol have indicated a high clearance (93 mL/kg/min), small volume of distribution (357 mL/kg), and a short half‑life (2.7 minutes). During infusions in animals, steady‑state plasma concentrations of tritium‑labeled epoprostenol were reached within 15 minutes and were proportional to infusion rates.

Metabolism

Tritium‑labeled epoprostenol has been administered to humans in order to identify the metabolic products of epoprostenol. Epoprostenol is metabolized to 2 primary metabolites: 6‑keto-PGF1α (formed by spontaneous degradation) and 6,15-diketo-13,14-dihydro-PGF1α (enzymatically formed), both of which have pharmacological activity orders of magnitude less than epoprostenol in animal test systems. The recovery of radioactivity in urine and feces over a 1‑week period was 82% and 4% of the administered dose, respectively. Fourteen additional minor metabolites have been isolated from urine, indicating that epoprostenol is extensively metabolized in humans.

Elimination

The in vitro half‑life of epoprostenol in human blood at 37°C and pH 7.4 is approximately 6 minutes; therefore, the in vivo half‑life of epoprostenol in humans is expected to be no greater than 6 minutes.

Drug Interaction Studies

In a pharmacokinetic substudy in patients with congestive heart failure receiving furosemide in whom therapy with FLOLAN was initiated, apparent oral clearance values for furosemide (n = 23) were decreased by 13% on the second day of therapy and returned to baseline values by Day 87. The change in furosemide clearance value is not likely to be clinically significant.

In a pharmacokinetic substudy in patients with congestive heart failure receiving digoxin in whom therapy with FLOLAN was initiated, apparent oral clearance values for digoxin (n = 30) were decreased by 15% on the second day of therapy and returned to baseline values by Day 87. Clinical significance of this interaction is not known.

13 NONCLINICAL TOXICOLOGY

13.1 Carcinogenesis, Mutagenesis, Impairment of Fertility

Long‑term studies in animals have not been performed to evaluate carcinogenic potential. A micronucleus test in rats revealed no evidence of mutagenicity. The Ames test and DNA elution tests were also negative, although the instability of epoprostenol makes the significance of these tests uncertain.

In a fertility/postnatal development study, epoprostenol sodium was administered subcutaneously to female rats for 2 weeks prior to mating through weaning and to male rats for 60 days prior to and through mating at an adult toxic dose of up to 100 mcg/kg/day (600 mcg/m^2/day, 2.5 times the MRHD based on body surface area). There was no effect on fertility in female or male rats.

14 CLINICAL STUDIES

14.1 Chronic Infusion in Idiopathic or Heritable PAH

Hemodynamic Effects

Chronic continuous infusions of FLOLAN in patients with idiopathic or heritable PAH were studied in 2 prospective, open, randomized trials of 8 and 12 weeks’ duration comparing FLOLAN plus conventional therapy with conventional therapy alone. Dosage of FLOLAN was determined as described in Dosage and Administration (2) and averaged 9.2 ng/kg/min at trials’ end. Conventional therapy varied among patients and included some or all of the following: anticoagulants in essentially all patients; oral vasodilators, diuretics, and digoxin in one-half to two-thirds of patients; and supplemental oxygen in about half the patients. Except for 2 NYHA Functional Class II patients, all patients were either functional Class III or Class IV. As results were similar in the 2 trials, the pooled results are described.

Chronic hemodynamic effects were generally similar to acute effects. Increases in CI, SV, and arterial oxygen saturation and decreases in PAPm, mean right atrial pressure (RAPm), TPR, and systemic vascular resistance (SVR) were observed in patients who received FLOLAN chronically compared with those who did not. Table 3 illustrates the treatment‑related hemodynamic changes in these patients after 8 or 12 weeks of treatment.

Table 3. Hemodynamics during Chronic Administration of FLOLAN in Patients with Idiopathic or Heritable PAH
 | Baseline |  | Mean Change from Baseline at End of Treatment Perioda
Hemodynamic; Parameter | FLOLAN; (n = 52) | Standard Therapy; (n = 54) | FLOLAN; (n = 48) | Standard Therapy; (n = 41)
CI; (L/min/m^2) | 2.0 | 2.0 | 0.3b | -0.1
PAPm; (mm Hg) | 60 | 60 | -5b | 1
PVR; (Wood U) | 16 | 17 | -4b | 1
SAPm; (mm Hg) | 89 | 91 | -4 | -3
SV; (mL/beat) | 44 | 43 | 6b | -1
TPR; (Wood U) | 20 | 21 | -5b | 1
CI = Cardiac index, PAPm = Mean pulmonary arterial pressure, PVR = Pulmonary vascular resistance, SAPm = Mean systemic arterial pressure, SV = Stroke volume, TPR = Total pulmonary resistance.
a At 8 weeks: FLOLAN n = 10, conventional therapy n = 11 (n is the number of patients with hemodynamic data).
At 12 weeks: FLOLAN n = 38, conventional therapy n = 30 (n is the number of patients with hemodynamic data).
b Denotes statistically significant difference between group receiving FLOLAN and group receiving conventional therapy.

These hemodynamic improvements appeared to persist when FLOLAN was administered for at least 36 months in an open, nonrandomized trial.

The acute hemodynamic response to FLOLAN did not correlate well with improvement in exercise tolerance or survival during chronic use of FLOLAN.

Clinical Effects

A statistically significant improvement was observed in exercise capacity, as measured by the 6‑minute walk test in patients receiving continuous intravenous FLOLAN plus conventional therapy (n = 52) for 8 or 12 weeks compared with those receiving conventional therapy alone (n = 54). Improvements were apparent as early as the first week of therapy. Increases in exercise capacity were accompanied by statistically significant improvement in dyspnea and fatigue, as measured by the Chronic Heart Failure Questionnaire and the Dyspnea Fatigue Index, respectively.

Survival was improved in NYHA Functional Class III and Class IV patients with idiopathic or heritable PAH treated with FLOLAN for 12 weeks in a multicenter, open, randomized, parallel trial. At the end of the treatment period, 8 of 40 (20%) patients receiving conventional therapy alone died, whereas none of the 41 patients receiving FLOLAN died (P = 0.003).

14.2 Chronic Infusion in PAH/SSD

Hemodynamic Effects

Chronic continuous infusions of FLOLAN in patients with PAH/SSD were studied in a prospective, open, randomized trial of 12 weeks’ duration comparing FLOLAN plus conventional therapy (n = 56) with conventional therapy alone (n = 55). Except for 5 NYHA Functional Class II patients, all patients were either functional Class III or Class IV. In the controlled 12-week trial in PAH/SSD, for example, the dose increased from a mean starting dose of 2.2 ng/kg/min. During the first 7 days of treatment, the dose was increased daily to a mean dose of 4.1 ng/kg/min on Day 7 of treatment. At the end of Week 12, the mean dose was 11.2 ng/kg/min. The mean incremental increase was 2 to 3 ng/kg/min every 3 weeks.

Conventional therapy varied among patients and included some or all of the following: anticoagulants in essentially all patients, supplemental oxygen and diuretics in two-thirds of the patients, oral vasodilators in 40% of the patients, and digoxin in a third of the patients. A statistically significant increase in CI and statistically significant decreases in PAPm, RAPm, PVR, and SAPm after 12 weeks of treatment were observed in patients who received FLOLAN chronically compared with those who did not. Table 4 illustrates the treatment-related hemodynamic changes in these patients after 12 weeks of treatment.

Table 4. Hemodynamics during Chronic Administration of FLOLAN in Patients with PAH/SSD
 | Baseline |  | Mean Change from Baseline at 12 Weeks
Hemodynamic; Parameter | FLOLAN; (n = 56) | Conventional Therapy; (n = 55) | FLOLAN; (n = 50) | Conventional Therapy; (n = 48)
CI; (L/min/m^2) | 1.9 | 2.2 | 0.5a | -0.1
PAPm; (mm Hg) | 51 | 49 | -5a | 1
RAPm; (mm Hg) | 13 | 11 | -1a | 1
PVR; (Wood U) | 14 | 11 | -5a | 1
SAPm; (mm Hg) | 93 | 89 | -8a | -1
CI = Cardiac index, PAPm = Mean pulmonary arterial pressure, RAPm = Mean right arterial pressure, PVR = Pulmonary vascular resistance, SAPm = Mean systemic arterial pressure.
a Denotes statistically significant difference between group receiving FLOLAN and group receiving conventional therapy (n is the number of patients with hemodynamic data).

Clinical Effects

Statistically significant improvement was observed in exercise capacity, as measured by the 6‑minute walk, in patients receiving continuous intravenous FLOLAN plus conventional therapy for 12 weeks compared with those receiving conventional therapy alone. Improvements were apparent in some patients at the end of the first week of therapy. Increases in exercise capacity were accompanied by statistically significant improvements in dyspnea and fatigue, as measured by the Borg Dyspnea Index and Dyspnea Fatigue Index. At Week 12, NYHA functional class improved in 21 of 51 (41%) patients treated with FLOLAN compared with none of the 48 patients treated with conventional therapy alone. However, more patients in both treatment groups (28/51 [55%] with FLOLAN and 35/48 [73%] with conventional therapy alone) showed no change in functional class, and 2/51 (4%) with FLOLAN and 13/48 (27%) with conventional therapy alone worsened.

No statistical difference in survival over 12 weeks was observed in patients with PAH/SSD treated with FLOLAN as compared with those receiving conventional therapy alone. At the end of the treatment period, 4 of 56 (7%) patients receiving FLOLAN died, whereas 5 of 55 (9%) patients receiving conventional therapy alone died.

14.3 Increased Mortality in Patients with Heart Failure Caused by Severe Left Ventricular Systolic Dysfunction

A large trial evaluating the effect of FLOLAN on survival in NYHA Class III and IV patients with congestive heart failure due to severe left ventricular systolic dysfunction was terminated after an interim analysis of 471 patients revealed a higher mortality in patients receiving FLOLAN plus conventional therapy than in those receiving conventional therapy alone. The chronic use of FLOLAN in patients with heart failure due to severe left ventricular systolic dysfunction is therefore contraindicated.

16 HOW SUPPLIED/STORAGE AND HANDLING

16.1 How Supplied

FLOLAN for injection is supplied as a sterile freeze‑dried powder in 17‑mL flint glass vials with gray butyl rubber closures.

pH 12 STERILE DILUENT for FLOLAN is supplied in plastic vials containing 50‑mL diluent with fluororesin‑faced butyl rubber closures with aluminum overseal and lavender plastic flip-off cap.

FLOLAN for injection | 0.5-mg (500,000 ng) per vial, carton of 1 | NDC 0173-0517-00
FLOLAN for injection | 1.5-mg (1,500,000 ng) per vial, carton of 1 | NDC 0173-0519-00
pH 12 STERILE DILUENT for FLOLAN | 50 mL per vial (NDC 0173-0857-01), carton of 2 | NDC 0173-0857-02

16.2 Storage and Handling

Proper storage and handling are essential to maintain the potency of FLOLAN for injection.

Unopened vials of FLOLAN powder are stable until the date indicated on the package when stored at room temperature, 15°C to 25°C (59°F to 77°F) and protected from light in the carton.

Unopened vials of pH 12 STERILE DILUENT for FLOLAN are stable until the date indicated on the package when stored at room temperature, 15°C to 25°C (59°F to 77°F). DO NOT FREEZE.

17 PATIENT COUNSELING INFORMATION

Advise the patient to read the FDA-approved patient labeling (Patient Information).

Advise patients:

- FLOLAN must be reconstituted only with pH 12 STERILE DILUENT for FLOLAN.
- Reconstituted solutions prepared with pH 12 STERILE DILUENT for FLOLAN do NOT require use with a cold pouch.
- FLOLAN is infused continuously through a permanent indwelling central venous catheter via a small, portable infusion pump. Thus, therapy with FLOLAN requires commitment by the patient to drug reconstitution, drug administration, and care of the permanent central venous catheter. Patients must adhere to sterile technique in preparing the drug and in the care of the catheter, and even brief interruptions in the delivery of FLOLAN may result in rapid symptomatic deterioration. A patient’s decision to receive FLOLAN should be based upon the understanding that there is a high likelihood that therapy with FLOLAN will be needed for prolonged periods, possibly years. Consider the patient's ability to accept and care for a permanent intravenous catheter and infusion pump.
- FLOLAN prepared with pH 12 STERILE DILUENT for FLOLAN must not be used with any preparation or administration materials containing PET or PETG. Only use materials provided by a healthcare provider or pharmacist.
- To adjust infusion rates of FLOLAN only under the direction of a physician.
- To avoid interruptions in drug delivery, the patient should have access to a backup infusion pump and intravenous infusion sets.
- To contact their healthcare providers if any unusual bruising or bleeding develops.

Trademark is owned by or licensed to the GSK group of companies.

GlaxoSmithKline

Durham, NC 27701

©2023 GSK group of companies or its licensor.

FLL:11PI

PATIENT INFORMATION

FLOLAN (flow-lan)

(epoprostenol sodium)

for injection, for intravenous use

What is FLOLAN?

FLOLAN is a prescription medicine used to treat people with certain types of pulmonary arterial hypertension (PAH), which is high blood pressure in the arteries of the lungs. FLOLAN can improve your ability to be physically active.

It is not known if FLOLAN is safe and effective in children.

Do not use FLOLAN if you:

- have certain types of heart failure. Talk to your healthcare provider before using FLOLAN if you have heart failure.
- are allergic to FLOLAN or any of the ingredients in FLOLAN. See the end of this leaflet for a complete list of ingredients in FLOLAN.

Before you use FLOLAN, tell your healthcare provider about all of your medical conditions, including if you:

- are allergic to any medicine.
- are pregnant or plan to become pregnant. It is not known if FLOLAN will harm your unborn baby. You and your healthcare provider should decide if you will use FLOLAN.
- are breastfeeding or plan to breastfeed. It is not known if FLOLAN passes into your breast milk. You and your healthcare provider should decide if you will take FLOLAN or breastfeed. You should not do both.

Tell your healthcare provider about all the medicines you take, including prescription and over-the-counter medicines, vitamins, and herbal supplements.

Especially tell your healthcare provider if you take:

- a “water pill” (diuretic)
- a medicine for high blood pressure (hypertension)
- a blood thinner medicine (antiplatelet or anticoagulant medicine)

Ask your healthcare provider or pharmacist for a list of these medicines, if you are not sure.

Know the medicines you take. Keep a list of your medicines with you to show your healthcare provider and pharmacist when you get a new medicine.

How should I use FLOLAN?

- FLOLAN should only be given by infusion through a catheter placed in a vein (intravenous infusion) using an infusion pump.
- Your first treatment will be given to you by your healthcare provider or nurse. This is so your healthcare provider can monitor you and find the best dose for you.
- If your healthcare provider decides that you or your caregiver can give infusions of FLOLAN at home, you or your caregiver will receive training on the right way to mix and infuse FLOLAN. Do not try to infuse FLOLAN until you have been shown the right way to infuse FLOLAN by your healthcare provider.
- Treatment will be needed for a long period of time, possibly years. You must be able to accept and care for a catheter and infusion pump in order to be treated with FLOLAN.
- Use FLOLAN exactly as your healthcare provider tells you to.
- Do not change your dose or stop your infusion without talking to your healthcare provider. Stopping FLOLAN suddenly can cause serious side effects.
- You should have a backup infusion pump and extra supplies needed for your infusion of FLOLAN.
- Follow your healthcare provider’s instructions for taking blood thinner medicines, if prescribed for you.
- Before you use FLOLAN, you must mix (reconstitute) FLOLAN powder with pH 12 STERILE DILUENT for FLOLAN (comes in a plastic bottle).
  - Do not mix FLOLAN with any other diluent. You must use pH 12 STERILE DILUENT for FLOLAN.
  - FLOLAN prepared with pH 12 STERILE DILUENT for FLOLAN must not be used with any preparation or administration materials containing polyethylene terephthalate (PET) or polyethylene terephthalate glycol (PETG). Only use materials provided by a healthcare provider or pharmacist.
See “How should I store and use FLOLAN?” for more information about how to use and store FLOLAN the right way.
- A mixed solution of FLOLAN is clear and colorless. Do not use FLOLAN if the mixed solution looks discolored or cloudy, or if the solution has flakes or particles in it.

Using more than the prescribed dose of FLOLAN can lead to death. If you use more than the prescribed dose of FLOLAN, call your healthcare provider or go to the nearest emergency room right away.

What are the possible side effects of FLOLAN?

FLOLAN can cause serious side effects, including:

- Fluid in your lungs (pulmonary edema). If you develop pulmonary edema after starting FLOLAN, your healthcare provider will stop your treatment and you should not receive FLOLAN again.
- Worsening symptoms of pulmonary arterial hypertension (PAH) with a sudden decrease in the dose of FLOLAN. Do not change your dose of FLOLAN or stop your infusion without talking to your healthcare provider. If you suddenly stop or decrease your dose of FLOLAN you may develop worsening symptoms of your PAH, including shortness of breath, dizziness, weakness, or loss of strength.
- Widening of your blood vessels (vasodilation). Vasodilation reactions can happen after you start FLOLAN. These reactions are common and may cause low blood pressure (hypotension), flushing, nausea, vomiting, dizziness, and headache. Your healthcare provider should check your blood pressure regularly during treatment with FLOLAN, especially when you start FLOLAN and after your dose is changed.
- Increased risk for bleeding. FLOLAN affects how well your blood clots, so your risk for bleeding is increased. This is especially true if you have other risk factors for bleeding. Tell your healthcare provider if you develop any unusual bruising or bleeding.

The most common side effects of FLOLAN include:

- dizziness
- jaw pain
- headache
- muscle or bone pain
- nausea or vomiting

These are not all the possible side effects of FLOLAN. For more information, ask your healthcare provider or pharmacist.

Call your doctor for medical advice about side effects. You may report side effects to FDA at 1-800-FDA-1088.

How should I store and use FLOLAN?

- Store FLOLAN powder at room temperature between 59°F to 77°F (15°C to 25°C).
- Protect FLOLAN powder from light. Keep unopened vial of FLOLAN in the carton until you are ready to mix.
- Store the pH 12 STERILE DILUENT for FLOLAN at room temperature, 59°F to 77°F (15°C to 25°C). Do not freeze.
- Vials of pH 12 STERILE DILUENT for FLOLAN are for one-time use only. Throw away any unused diluent.
- Throw away any vials of FLOLAN powder and pH 12 STERILE DILUENT for FLOLAN that are out of date or that you no longer need.

How to store mixed solutions of FLOLAN:

- Once FLOLAN and the diluent are mixed together, you may use right away or store in the refrigerator. Refrigerate at 36°F to 46°F (2°C to 8°C).
- Protect the mixed solution of FLOLAN from light until you are ready to use it.
- Do not freeze mixed solutions. Throw away any mixed solution that has been frozen.
- Freshly prepared mixed solutions may be stored in the refrigerator for up to 8 days.
Mixed solutions (freshly prepared or taken out of the refrigerator) are stable for up to 48 hours at 77°F (25°C), up to 36 hours at 86°F (30°C), up to 24 hours at 95°F (35°C) or up to 12 hours at 104°F (40°C). Discard any unused solution after these times.
- FLOLAN mixed with pH 12 STERILE DILUENT for FLOLAN does not require use with a cold pouch.
- Throw away any mixed solution if it has been refrigerated for more than 8 days.

Keep FLOLAN and all medicines out of the reach of children.

General information about the safe and effective use of FLOLAN

Medicines are sometimes prescribed for purposes other than those listed in a Patient Information leaflet. Do not use FLOLAN for a condition for which it was not prescribed. Do not give FLOLAN to other people, even if they have the same symptoms that you have. It may harm them.

This leaflet summarizes the most important information about FLOLAN. You can ask your healthcare provider or pharmacist for information about FLOLAN that is written for health professionals.

What are the ingredients in FLOLAN?

Active ingredient: epoprostenol sodium.

Inactive ingredients: glycine, mannitol, sodium chloride. Sodium hydroxide may have been added.

The pH 12 STERILE DILUENT for FLOLAN contains: glycine, sodium chloride, sodium hydroxide, and Water for Injection.

GlaxoSmithKline

Durham, NC 27701

Trademark is owned by or licensed to the GSK group of companies.

©2023 GSK group of companies or its licensor.

FLL:7PIL

This Patient Information has been approved by the U.S. Food and Drug Administration. Revised: 10/2023

PACKAGE LABEL

PRINCIPAL DISPLAY PANEL

NDC 0173-0517-00

FLOLAN

(epoprostenol sodium)

for Injection

0.5 mg/vial (500,000 ng/vial)

Must be reconstituted. For intravenous infusion after dilution.

Note: Use only pH 12 STERILE DILUENT for FLOLAN for reconstitution and dilution.

Rx only

Single-Use Vial

Each vial contains epoprostenol sodium equivalent to 0.5 mg (500,000 ng) epoprostenol, 3.76 mg glycine, 2.93 mg sodium chloride, and 50 mg mannitol. Sodium hydroxide may have been added to adjust pH.

Usual Dose: See prescribing information.

Store at 15o and 25o C (59o to 77oF).

Protect from light.

Do not accept if plastic overseal is missing or not securely fitted.

GlaxoSmithKline

Durham, NC 27701

Rev. 12/23

62000000091775

PACKAGE LABEL

PRINCIPAL DISPLAY PANEL

NDC 0173-0519-00

FLOLAN

(epoprostenol sodium)

for Injection

1.5 mg/vial (1,500,000 ng/vial)

Must be reconstituted. For intravenous infusion after dilution.

Note: Use only pH 12 STERILE DILUENT for FLOLAN for reconstitution and dilution.

Rx only

Single-Use Vial

Each vial contains epoprostenol sodium equivalent to 1.5 mg (1,500,000 ng) epoprostenol, 3.76 mg glycine, 2.93 mg sodium chloride, and 50 mg mannitol. Sodium hydroxide may have been added to adjust pH.

Usual Dose: See prescribing information.

Store at 15o and 25o C (59o to 77oF).

Protect from light.

Do not accept if plastic overseal is missing or not securely fitted.

GlaxoSmithKline

Durham, NC 27701

Rev. 12/23

62000000091772

PACKAGE LABEL

PRINCIPAL DISPLAY PANEL

NDC 0173-0857-02

pH 12 Sterile Diluent for FLOLAN

Rx only

Use only with FLOLAN (epoprostenol sodium) for Injection

Single-Dose Vial. Discard Unused Portion.

2 vials, each vial contains 50 mL

GSK

Made in England

©2023 GSK group of companies or its licensor.

Rev. 09/23
62000000090121